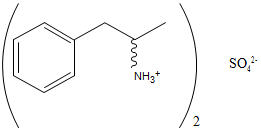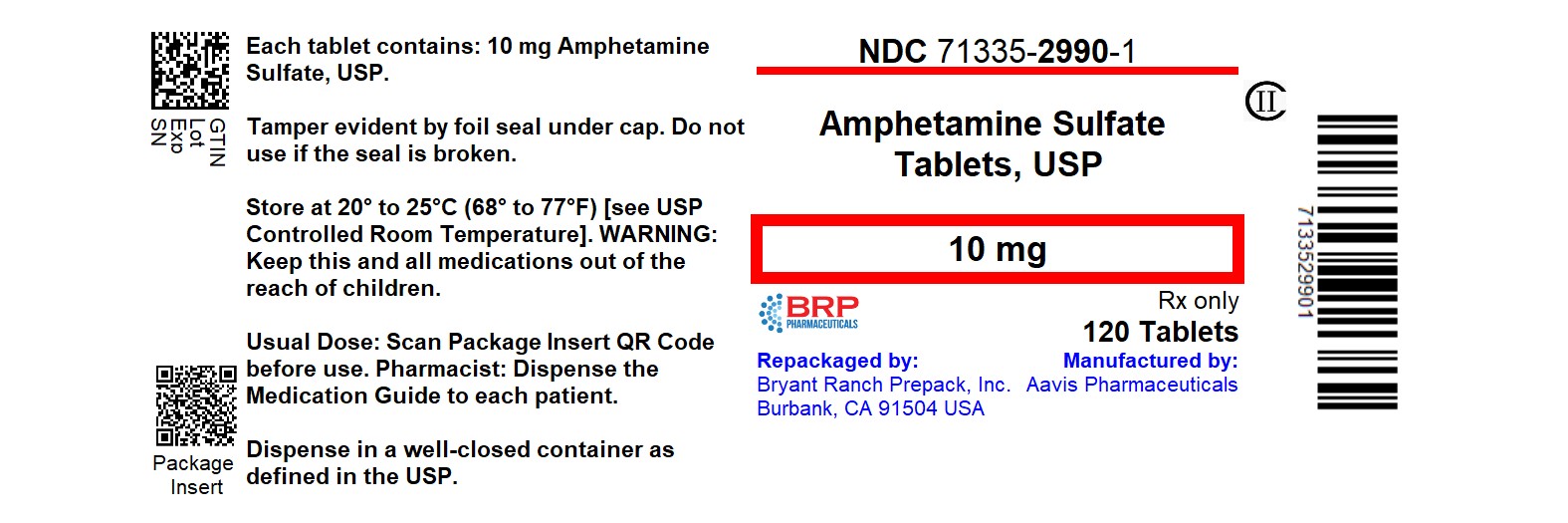 DRUG LABEL: AMPHETAMINE SULFATE
NDC: 71335-2990 | Form: TABLET
Manufacturer: Bryant Ranch Prepack
Category: prescription | Type: HUMAN PRESCRIPTION DRUG LABEL
Date: 20260204
DEA Schedule: CII

ACTIVE INGREDIENTS: AMPHETAMINE SULFATE 10 mg/1 1
INACTIVE INGREDIENTS: STEARIC ACID; MICROCRYSTALLINE CELLULOSE; SILICON DIOXIDE; FD&C BLUE NO. 1 ALUMINUM LAKE; CROSPOVIDONE

Amphetamine Sulfate Tablets, USP CII

WARNING: ABUSE, MISUSE, AND ADDICTION

Amphetamine sulfate has a high potential for abuse and misuse, which can lead to the development of a substance use disorder, including addiction. Misuse and abuse of CNS stimulants, including amphetamine sulfate, can result in overdose and death (see OVERDOSAGE), and this risk is increased with higher doses or unapproved methods of administration, such as snorting or injection.

Before prescribing amphetaminesulfate, assess each patient's risk for abuse, misuse, and addiction. Educate patients and their families about these risks, proper storage of the drug, and proper disposal of any unused drug. Throughout amphetamine sulfate treatment, reassess each patient's risk of abuse, misuse, and addiction and frequently monitor for signs and symptoms of abuse, misuse, and addiction (see WARNINGS and DRUG ABUSE AND DEPENDENCE).

DESCRIPTION

Amphetamine Sulfate is a sympathomimetic amino of the amphetamine group. It is a white, odorless crystalline powder. It has a slightly bitter taste. Its solutions are acid to litmus, having a pH of 5 to 8. It is freely soluble in water, slightly soluble in alcohol and practically insoluble in ether.

Each tablet, for oral administration contains 5 mg or 10 mg of amphetamine sulfate. Each tablet also contains the following inactive ingredients: crospovidone, silicified microcrystalline cellulose and stearic acid. The 10 mg tablet also contains FD&C Blue #1 Alum Lake.

Structural Formula:

C18H28N2SO4 MW 368.49

CLINICAL PHARMACOLOGY

Amphetamines are non-catecholamine, sympathomimetic amines with CNS stimulant activity. Peripheral actions include elevations of systolic and diastolic blood pressures, and weak bronchodilator, and respiratory stimulant action.

Amphetamine, as the racemic form, differs from dextroamphetamine in a number of ways. The l-isomer is more potent than the d-isomer in cardiovascular activity, but much less potent in causing CNS excitatory effects. The racemic mixture also is less effective as an appetite suppressant when compared to dextroamphetamine. There is neither specific evidence which clearly establishes the mechanism whereby amphetamines produce mental and behavioral effects in children, nor conclusive evidence regarding how those effects relate to the condition of the central nervous system.

Drugs in this class used in obesity are commonly known as "anorectics" or "anorexigenics." It has not been established, however, that the action of such drugs in treating obesity is primarily one of appetite suppression. Other central nervous system actions or metabolic effects, may be involved, for example. Adult obese subjects instructed in dietary management and treated with "anorectic" drugs lose more weight on the average than these treated with placebo and diet, as determined in relatively short- term clinical trials.

The magnitude of increased weight loss of drug-treated patients over placebo-treated patients is only a fraction of a pound a week. The rate of weight loss is greatest in the first weeks of therapy for both drug and placebo subjects and tends to decrease in succeeding weeks. The origins of the increased weight loss due to the various possible drug effects are not established. The amount of weight loss associated with the use of an "anorectic" drug varies from trial to trial, and the increased weight loss appears to be related in part to variables other than the drug prescribed, such as the physician-investigator, the population treated, and the diet prescribed. Studies do not permit conclusions as to the relative importance of the drug and nondrug factors on weight loss.

The natural history of obesity is measured in years, whereas the studies cited are restricted to few weeks duration; thus, the total impact of drug-induced weight loss over that of diet alone must be considered clinically limited.

INDICATIONS AND USAGE

Amphetamine sulfate tablets, USP 5 mg and 10 mg are indicated for:

1. Narcolepsy
2. Attention Deficit-Disorder with Hyperactivity as an integral part of a total treatment program which typically includes other remedial measures (psychological, educational, social) for a stabilizing effect in children with behavioral syndrome characterized by the following group of developmentally inappropriate symptoms: moderate to severe distractibility, short attention span, hyperactivity, emotional lability, and impulsivity. The diagnosis of the syndrome should not be made with finality when these symptoms are only of comparatively recent origin. Nonlocalizing (soft) neurological signs, learning disability, and abnormal EEG may or may not be present, and a diagnosis of central nervous system dysfunction may or not be warranted.
3. Exogenous Obesity as a short term (a few weeks) adjunct in a regimen of weight reduction based on caloric restriction for patients refractory to alternative therapy, e.g., repeated diets, group programs, and other drugs. The limited usefulness of amphetamines (see CLINICAL PHARMACOLOGY) should be weighed against possible risks inherent in use of the drug, such as those described below.

CONTRAINDICATIONS

- Known hypersensitivity to amphetamine products.
- During or within 14 days following the administration of monoamine oxidase inhibitors (hypertensive crises may result) (see WARNINGS).

WARNINGS

Abuse, Misuse, and Addiction

Amphetamine sulfate has a high potential for abuse and misuse. The use of Amphetamine sulfate exposes individuals to the risks of abuse and misuse, which can lead to the development of a substance use disorder, including addiction. Amphetamine sulfate can be diverted for non-medical use into illicit channels or distribution (see DRUG ABUSE AND DEPENDENCE). Misuse and abuse of CNS stimulants, including Amphetamine sulfate, can result in overdose and death (see OVERDOSAGE), and this risk is increased with higher doses or unapproved methods of administration, such as snorting or injection.

Before prescribing Amphetamine sulfate, assess each patient's risk for abuse, misuse, and addiction. Educate patients and their families about these risks and proper disposal of any unused drug. Advise patients to store amphetamine sulfate in a safe place, preferably locked, and instruct patients to not give Amphetamine sulfate to anyone else. Throughout Amphetamine sulfate treatment, reassess each patient's risk of abuse, misuse, and addiction and frequently monitor for signs and symptoms of abuse, misuse, and addiction.

Risks to Patients with Serious Cardiac Disease

Sudden death has been reported in patients with structural cardiac abnormalities or other serious cardiac disease who are treated with CNS stimulants at the recommended ADHD dosages.

Avoid amphetamine sulfate use in patients with known structural cardiac abnormalities, cardiomyopathy, serious cardiac arrhythmia, coronary artery disease, or other serious cardiac disease.

Increased Blood Pressure and Heart Rate

CNS stimulants cause an increase in blood pressure (mean increase about 2 to 4 mm Hg) and heart rate (mean increase about 3 to 6 bpm). Monitor all patients for potential tachycardia and hypertension.

Psychiatric Adverse Reactions

Exacerbation of Pre-Existing Psychosis

CNS stimulants may exacerbate symptoms of behavior disturbance and thought disorder

in patients with a pre-existing psychotic disorder.

Induction of a Manic Episode in Patients with Bipolar Disorder

CNS stimulants may induce a manic or mixed episode in patients. Prior to initiating amphetamine sulfate, screen patients for risk factors for developing a manic episode (e.g., comorbid or history of depressive symptoms or a family history of suicide, bipolar disorder, or depression).

New Psychotic or Manic Symptoms

CNS stimulants, at recommended doses, may cause psychotic or manic symptoms (e.g., hallucinations, delusional thinking, or mania) in patients without a prior history of psychotic illness or mania. In a pooled analysis of multiple short-term, placebo-controlled studies of CNS stimulants, psychotic or manic symptoms occurred in approximately 0.1% of CNS stimulant-treated patients, compared with 0% of placebo-treated patients. If such symptoms occur, consider discontinuing amphetamine sulfate.

Long-Term Suppression of Growth in Pediatric Patients

CNS stimulants have been associated with weight loss and slowing of growth rate in pediatric patients. Closely monitor growth (weight and height) in amphetamine sulfate-treated pediatric patients treated with CNS stimulants.

Pediatric patients not growing or gaining height or weight as expected may need to have their treatment interrupted (see PRECAUTIONS, PEDIATRIC USE).

Seizures

There is some clinical evidence that stimulants may lower the convulsive threshold in patients with prior history of seizures, in patients with prior EEG abnormalities in absence of seizures, and, very rarely, in patients without a history of seizures and no prior EEG evidence of seizures. In the presence of seizures, the drug should be discontinued.

Peripheral Vasculopathy, including Raynaud's phenomenon

Stimulants, including amphetamine sulfate, used to treat ADHD are associated with peripheral vasculopathy, including Raynaud's phenomenon. Signs and symptoms are usually intermittent and mild; however, very rare sequelae include digital ulceration and/or soft tissue breakdown. Effects of peripheral vasculopathy, including Raynaud's phenomenon, were observed in post-marketing reports and at the therapeutic dosages of CNS stimulants in all age groups throughout the course of treatment. Signs and symptoms generally improved after dosage reduction or discontinuation of the CNS stimulant.

Careful observation for digital changes is necessary during amphetamine sulfate treatment. Further clinical evaluation (e.g., rheumatology referral) may be appropriate for patients who develop signs or symptoms of peripheral vasculopathy.

Serotonin Syndrome

Serotonin syndrome, a potentially life-threatening reaction, may occur when amphetamines are used in combination with other drugs that affect the serotonergic neurotransmitter systems such as monoamine oxidase inhibitors (MAOIs), selective serotonin reuptake inhibitors (SSRIs), serotonin norepinephrine reuptake inhibitors (SNRIs), triptans, tricyclic antidepressants, fentanyl, lithium, tramadol, tryptophan, buspirone, and St. John's Wort (see DRUG INTERACTIONS). The co-administration with cytochrome P450 (CYP2D6) inhibitors may also increase the risk with increased exposure to amphetamine sulfate. In these situations, consider an alternative non-serotonergic drug or an alternative drug that does not inhibit CYP2D6 (see DRUG INTERACTIONS).

Serotonin syndrome symptoms may include mental status changes (e.g., agitation, hallucinations, delirium, and coma), autonomic instability (e.g., tachycardia, labile blood pressure, dizziness, diaphoresis, flushing, hyperthermia), neuromuscular symptoms (e.g., tremor, rigidity, myoclonus, hyperreflexia, incoordination), seizures, and/or gastrointestinal symptoms (e.g., nausea, vomiting, diarrhea).

Concomitant use of amphetamine sulfate with MAOI drugs is contraindicated (see CONTRAINDICATIONS).

Discontinue treatment with amphetamine sulfate and any concomitant serotonergic agents immediately if the above symptoms occur, and initiate supportive symptomatic treatment. If concomitant use of amphetamine sulfate with other serotonergic drugs or CYP2D6 inhibitors is clinically warranted, initiate amphetamine sulfate with lower doses, monitor patients for the emergence of serotonin syndrome during drug initiation or titration, and inform patients of the increased risk for serotonin syndrome.

Motor and Verbal Tics, and Worsening of Tourette's Syndrome

CNS stimulants, including amphetamine sulfate, have been associated with the onset or exacerbation of motor and verbal tics. Worsening of Tourette's syndrome has also been reported. Assess the family history and clinically evaluate patients for tics or Tourette's syndrome before initiating amphetamine sulfate. Regularly monitor patients for the emergence or worsening of tics or Tourette's syndrome with amphetamine sulfate, and discontinue treatment if clinically appropriate.

PRECAUTIONS

General

Caution is to be exercised in prescribing amphetamines for patients with even mild hypertension.

Information for Patients

Advise the patient to read the FDA-approved patient labeling (Medication Guide).

Abuse, Misuse, and Addiction

Educate patients and their families about the risks of abuse, misuse, and addiction of amphetamine sulfate, which can lead to overdose and death, and proper disposal of any unused drug (see WARNINGS, DRUG ABUSE AND DEPENDENCE, andOVERDOSAGE). Advise patients to store amphetamine sulfate in a safe place, preferably locked, and instruct patients to not give amphetamine sulfate to anyone else.

Risks to Patients with Serious Cardiac Disease

Advise patients that there are potential risks to patients with serious cardiac disease, including sudden death, with amphetamine sulfate use. Instruct patients to contact a healthcare provider immediately if they develop symptoms such as exertional chest pain, unexplained syncope, or other symptoms suggestive of cardiac disease (see WARNINGS).

Increased Blood Pressure and Heart Rate

Advise patients that amphetamine sulfate can elevate blood pressure and heart rate (see WARNINGS).

Psychiatric Adverse Reactions

Advise patients that amphetamine sulfate, at recommended doses, can cause psychotic or manic symptoms, even in patients without prior history of psychotic symptoms or mania (see WARNINGS).

Long-Term Suppression of Growth in Pediatric Patients

Advise patients that amphetamine sulfate, may cause slowing of growth including weight loss (see WARNINGS).

Circulation problems in fingers and toes [Peripheral vasculopathy, including Raynaud's phenomenon]

- Instruct patients beginning treatment with amphetamine sulfate about the risk of peripheral vasculopathy, including Raynaud's Phenomenon, and associated signs and symptoms: fingers or toes may feel numb, cool, painful, and/or may change color from pale, to blue, to red.
- Instruct patients to report to their physician any new numbness, pain, skin color change, or sensitivity to temperature in fingers or toes.
- Instruct patients to call their physician immediately with any signs of unexplained wounds appearing on fingers or toes while taking amphetamine sulfate.
- Further clinical evaluation (e.g., rheumatology referral) may be appropriate for certain patients.

Serotonin Syndrome

Caution patients about the risk of serotonin syndrome with concomitant use of amphetamine sulfate and other serotonergic drugs including SSRIs, SNRIs, triptans, tricyclic antidepressants, fentanyl, lithium, tramadol, tryptophan, buspirone, St. John's Wort, and with drugs that impair metabolism of serotonin (in particular MAOIs, both those intended to treat psychiatric disorders and also others such as linezolid [see CONTRAINDICATIONS, WARNINGS, and DRUG INTERACTIONS]. Advise patients to contact their healthcare provider or report to the emergency room if they experience signs or symptoms of serotonin syndrome.

Motor and Verbal Tics, and Worsening of Tourette's Syndrome

Advise patients that motor and verbal tics and worsening of Tourette's Syndrome may occur during treatment with amphetamine sulfate. Instruct the patients to notify their healthcare provider if emergence or worsening of tics or Tourette's syndrome occurs (see WARNINGS).

Amphetamines may impair the ability of the patient to engage in potentially hazardous activities such as operating machinery or vehicle; the patient should therefore be cautioned accordingly.

Drug Interactions

MAO inhibitors- MAOI antidepressants, as well as a metabolic of furazolidone, slow amphetamine metabolism. This slowing potentiates amphetamines, increasing their effect on the release of norepinephrine and other monoamines from adrenergic nerve endings; this can cause headaches and other signs of hypertensive crisis. A variety of neurological toxic effects and malignant hyperpyrexia can occur, sometimes with fatal results.

Serotonergic Drugs- The concomitant use of amphetamine sulfate and serotonergic drugs increases the risk of serotonin syndrome. Initiate with lower doses and monitor patients for signs and symptoms of serotonin syndrome, particularly during amphetamine sulfate initiation or dosage increase. If serotonin syndrome occurs, discontinue amphetamine sulfate and the concomitant serotonergic drug(s) (see WARNING and PRECAUTIONS).

CYP2D6 Inhibitors- The concomitant use of amphetamine sulfate and CYP2D6 inhibitors may increase the exposure of amphetamine sulfate compared to the use of the drug alone and increase the risk of serotonin syndrome. Initiate with lower doses and monitor patients for signs and symptoms of serotonin syndrome particularly during amphetamine sulfate initiation and after a dosage increase. If serotonin syndrome occurs, discontinue amphetamine sulfate and the CYP2D6 inhibitor (see WARNING, OVERDOSAGE). Examples of CYP2D6 Inhibitors include paroxetine and fluoxetine (also serotonergic drugs), quinidine, ritonavir.

Acidifying agents- Gastrointestinal acidifying agents (guanethidine, reserpine, glutamic acid HCl, ascorbic acid, fruit juices, etc.) lower absorption of amphetamines. Urinary acidifying agents (ammonium chloride, sodium acid phosphate, etc.) increase concentration of the ionized species of the amphetamine molecule, thereby increasing urinary excretion. Both groups of agents lower blood levels and efficacy of amphetamines.

Adrenergic blockers- Adrenergic blockers are inhibited by amphetamines.

Alkalinizing agents- Gastrointestinal alkalinizing agents (sodium bicarbonate, etc.) increase absorption of amphetamines. Urinary alkalinizing agents (acetazolamide, some thiazides) increase the concentration of the non-ionized species of the amphetamine molecule, thereby decreasing urinary excretion. Both groups of agents increase blood levels and therefore potentiate the action of amphetamines.

Antidepressants tricyclic- Amphetamines may enhance the activity of tricyclic or sympathomimetic agents; d-amphetamine with desipramine or protriptyline and possibly other tricyclics cause striking and sustained increases in the concentration of d- amphetamine in the brain; cardiovascular effects can be potentiated.

Antihistamines- Amphetamines may counteract the sedative effect of antihistamines.

Antihypertensives- Amphetamines may antagonize the hypotensive effects of antihypertensives.

Chlorpromazine- Chlorpromazine blocks dopamine and norepinephrine reuptake, thus inhibiting the central stimulant effects of amphetamine, and can be used to treat amphetamine poisoning.

Ethosuximide- Amphetamines may delay intestinal absorption of ethosuximide.

Haloperidol- Haloperidol blocks dopamine and norepinephrine reuptake, thus inhibiting the central stimulant effects of amphetamines.

Lithium carbonate- The antiobesity and stimulatory effects of amphetamines may be inhibited by lithium carbonate.

Meperidine- Amphetamines potentiate the analgesic effect of meperidine.

Methenamine therapy- Urinary excretion of amphetamines is increased, and efficacy is reduced by acidifying agents used in methenamine therapy.

Norepinephrine- Amphetamines enhance the adrenergic effect of norepinephrine.

Phenobarbital- Amphetamines may delay intestinal absorption of Phenobarbital. Co-administration of phenobarbital may produce a synergistic anticonvulsant action.

Phenytoin- Amphetamines may delay intestinal absorption of phenytoin; co-administration of phenytoin may produce a synergistic anticonvulsant action.

Propoxyphene- In cases of propoxyphene overdosage, amphetamine CNS stimulation is potentiated and fatal convulsions can occur.

Veratrum alkaloids- Amphetamines inhibit the hypotensive effect of veratrum alkaloids.

Drug/Laboratory Test interactions

Amphetamines can cause a significant elevation in plasma corticosteroid levels. This increase is greatest in the evening. Amphetamines may interfere with urinary steroid determinations.

Carcinogenesis/Mutagenesis

Mutagenicity studies and long term studies in animals to determine the carcinogenic potential of amphetamine sulfate have not been performed.

Pregnancy

Teratogenic Effects

Dextroamphetamine sulfate has been shown to have embryotoxic and teratogenic effects when administered to A/Jax mice and C57BL mice in doses approximately 41 times the maximum human dose. Embryotoxic effects were not seen in New Zealand white rabbits given the drug in doses 7 times the human dose nor in rats given 12.5 times the maximum human dose. There are no adequate and well-controlled studies in pregnant women. Amphetamine sulfate should be used during pregnancy only if the potential benefit justifies the potential risk to the fetus.

Nonteratogenic Effects

Infants born to mothers dependent on amphetamines have an increased risk of premature delivery and low birth weight. Also, these infants may experience symptoms of withdrawal as demonstrated by dysphoria, including agitation, and significant lassitude.

Nursing Mothers

Amphetamines are excreted in human milk. Mothers taking amphetamines should be advised to refrain from nursing.

Pediatric Use

Long-term effects of amphetamines in children have not been well established.

Amphetamines are not recommended for use as anorectic agents in children under 12 years of age, or in children under 3 years of age with Attention Deficit Disorder with Hyperactivity described under INDICATIONS AND USAGE.

Clinical experience suggests that in psychotic children, administration of amphetamines may exacerbate symptoms of behavior disturbance and thought disorder.

Data is inadequate to determine whether chronic administration of amphetamines may be associated with growth inhibition; therefore growth should be monitored during treatment. Drug Treatment is not indicated in all cases of Attention Deficit Disorder with Hyperactivity and should be considered only in light of the complete history and evaluation of the child. The decision to prescribe amphetamines should depend on the physician's assessment of the chronicity and severity of the child's symptoms and their appropriateness for his/her age. Prescription should not depend solely on the presence of one or more of the behavioral characteristics.

When these symptoms are associated with acute stress reactions, treatment with amphetamines is usually not indicated.

ADVERSE REACTIONS

Cardiovascular

Palpitations, tachycardia, elevation of blood pressure. There have been isolated reports of cardiomyopathy associated with chronic amphetamine use.

Central Nervous System

Psychotic episodes at recommended doses (rare), overstimulation, restlessness, dizziness, insomnia, euphoria, dyskinesia, dysphoria, tremor, headache, exacerbation of motor and verbal tics and Tourette's syndrome.

Gastrointestinal

Dryness of the mouth, unpleasant taste, diarrhea, constipation, intestinal ischemia and other gastrointestinal disturbances. Anorexia and weight loss may occur as undesirable effects when amphetamines are used for other than the anorectic effect.

Allergic

Urticaria

Endocrine

Impotence, changes in libido, and frequent or prolonged erections.

Musculoskeletal

Rhabdomyolysis

DRUG ABUSE AND DEPENDENCE

Controlled Substance

Amphetamine sulfate tablets contain amphetamine, a Schedule II controlled substance.

Abuse

Amphetamine sulfate has a high potential for abuse and misuse which can lead to the development of a substance use disorder, including addiction (see WARNINGS). Amphetamine sulfate can be diverted for non-medical use into illicit channels or distribution.

Abuse is the intentional non-therapeutic use of a drug, even once, to achieve a desired psychological or physiological effect. Misuse is the intentional use, for therapeutic purposes, of a drug by an individual in a way other than prescribed by a health care provider or for whom it was not prescribed. Drug addiction is a cluster of behavioral, cognitive, and physiological phenomena that may include a strong desire to take the drug, difficulties in controlling drug use (e.g., continuing drug use despite harmful consequences, giving a higher priority to drug use than other activities and obligations), and possible tolerance or physical dependence.

Misuse and abuse of amphetamines may cause increased heart rate, respiratory rate, or blood pressure; sweating; dilated pupils; hyperactivity; restlessness; insomnia; decreased appetite; loss of coordination; tremors; flushed skin; vomiting; and/or abdominal pain. Anxiety, psychosis, hostility, aggression, and suicidal or homicidal ideation have also been observed with CNS stimulants abuse and/or misuse. Misuse and abuse of CNS stimulants, including amphetamine sulfate, can result in overdose and death (see OVERDOSAGE), and this risk is increased with higher doses or unapproved methods of administration, such as snorting or injection.

Dependence

Physical Dependence

Amphetamine sulfate may produce physical dependence. Physical dependence is a state that develops as a result of physiological adaptation in response to repeated drug use, manifested by withdrawal signs and symptoms after abrupt discontinuation or a significant dose reduction of a drug.

Withdrawal signs and symptoms after abrupt discontinuation or dose reduction following prolonged use of CNS stimulants including Amphetamine sulfate include dysphoric mood; depression; fatigue; vivid, unpleasant dreams; insomnia or hypersomnia; increased appetite; and psychomotor retardation or agitation.

Tolerance

Amphetamine sulfate may produce tolerance. Tolerance is a physiological state characterized by a reduced response to a drug after repeated administration (i.e., a higher dose of a drug is required to produce the same effect that was once obtained at a lower dose).

OVERDOSAGE

Clinical Effects of Overdose

Overdose of CNS stimulants is characterized by the following sympathomimetic effects:

- Cardiovascular effects including tachyarrhythmias, and hypertension or hypotension. Vasospasm, myocardial infarction, or aortic dissection may precipitate sudden cardiac death. Takotsubo cardiomyopathy may develop.
- CNS effects including psychomotor agitation, confusion, and hallucinations. Serotonin syndrome, seizures, cerebral vascular accidents, and coma may occur.
- Life-threatening hyperthermia (temperatures greater than 104°F) and rhabdomyolysis may develop.

Overdose Management

Consider the possibility of multiple drug ingestion. D-amphetamine is not dialyzable. Consider contacting the Poison Help line (1-800-222-1222) or a medical toxicologist for additional overdose management recommendations.

DOSAGE AND ADMINISTRATION

Regardless of indication, amphetamine should be administered at the lowest effective dosage and dosage should be individually adjusted. Late evening doses should be avoided because of resulting insomnia.

Narcolepsy

Usual dose is 5 to 60 milligrams per day in divided doses depending on the individual patient response.

Narcolepsy seldom occurs in children under 12 years of age; however, when it does, amphetamine sulfate tablets, USP may be used. The suggested initial dose for patients aged 6 to 12 is 5 mg daily; daily dose may be raised in increments of 5 mg at weekly intervals until optimal response obtained. In patients 12 years of age and older, start with 10 mg daily; daily dosage may be raised in increments of 10 mg at weekly intervals until optimal response is obtained. If bothersome adverse reactions appear (e.g., insomnia or anorexia) dosage should be reduced. Give the first dose on awakening; additional doses (5 or 10 mg) at intervals of 4 to 6 hours.

Attention Deficit Disorder with Hyperactivity

Not recommended for children under 3 years of age.

In children from 3 to 5 years of age, start with 2.5 mg daily; daily dosage may be raised in increments of 2.5 mg at weekly intervals until optimal response is obtained.

In children 6 years of age or older, start with 5 mg once or twice daily; daily dosage may be raised in increments of 5 mg at weekly intervals until optimal response is obtained. Only in rare cases will it be necessary to exceed a total of 40 milligrams per day.

With tablets give first dose on awakening; additional doses (1 to 2) at intervals of 4 to 6 hours.

Where possible, drug administration should be interrupted occasionally to determine if there is a recurrence of behavioral symptoms sufficient to require continued therapy.

Prior to treating patients with amphetamine sulfate assess:

- for the presence of cardiac disease (i.e., perform a careful history, family history of sudden death or ventricular arrhythmia, and physical exam) (see WARNINGS).
- the family history and clinically evaluate patients for motor or verbal tics or Tourette's syndrome (see WARNINGS).

Exogenous Obesity

Usual dosage is up to 30 mg daily, taken in divided doses of 5 to 10 mg, 30 to 60 minutes before meals. Not recommended for this use in children under 12 years of age.

HOW SUPPLIED

Amphetamine Sulfate Tablets, USP are functionally scored and supplied as follows:

10 mg: Blue, round shaped tablet, scored, debossed "A25" on one side, and quadrisect on the other side.

- NDC 71335-2990-1: 120 Tablets in a BOTTLE

Store at 20° to 25°C (68° to 77°F). [See USP Controlled Room Temperature.] Dispense in a well-closed container, as defined in the USP.

Repackaged/Relabeled by:
Bryant Ranch Prepack
Burbank, CA 91504

MEDICATION GUIDE

Amphetamine sulfate tablets, CII
(am fet' a meen sul' fate)

What is the most important information I should know about amphetamine sulfate?
Amphetamine Sulfate may cause serious side effects, including:

- Abuse, misuse, and addiction. Amphetamine sulfate has a high chance for abuse and misuse and may lead to substance use problems, including addiction. Misuse and abuse of Amphetamine sulfate, other amphetamine-containing medicines, and methylphenidate, can lead to overdose and death. The risk of overdose and death is increased with higher doses of Amphetamine sulfate or when it is used in ways that are not approved, such as snorting or injection.
  - Your healthcare provider should check you or your child's risk for abuse, misuse, and addiction before starting treatment with amphetamine sulfate and will monitor you or your child during treatment.
  - Amphetamine sulfate may lead to physical dependence after prolonged use, even if taken as directed by your healthcare provider.
  - Do not give amphetamine sulfate to anyone else. See "What is Amphetamine sulfate?" for more information.
  - Keep amphetamine sulfate in a safe place and properly dispose of unused medicine. See "How should I store amphetamine sulfate tablets?" for more information.
  - Tell your healthcare provider if you or your child have ever abused or been dependent on alcohol, prescription medicines, or street drugs.

Risks for people with serious heart disease

- Sudden death has happened in people who have heart defects or other serious heart disease.

Your healthcare provider should check you or your child carefully for heart problems before starting amphetamine sulfate.
Tell your healthcare provider if you or your child have any heart problems, heart disease, or heart defects.
Call your healthcare provider or go to the nearest hospital emergency room right away if you or your child have any signs of heart problems such as chest pain, shortness of breath, or fainting during treatment with amphetamine sulfate.

- Increased blood pressure and heart rate.

Your healthcare provider should check you or your child's blood pressure and heart rate regularly during treatment with amphetamine sulfate.

- Mental (psychiatric) problems, including:
  - new or worse behavior and thought problems
  - new or worse bipolar illness
  - new psychotic symptoms (such as hearing voices, or seeing or believing things that are not real) or new manic symptoms

Tell your healthcare provider about any mental problems you or your child have, or about a family history of suicide, bipolar illness, or depression.
Call your healthcare provider right away if you or your child have any new or worsening mental symptoms or problems during treatment with amphetamine sulfate, especially hearing voices, seeing or believing things that are not real, or new manic symptoms.

What are amphetamine sulfate tablets?
Amphetamine sulfate tablets are a central nervous system (CNS) stimulant prescription medicine used for the treatment of:

- a sleep disorder called narcolepsy.
- Attention-Deficit Hyperactivity Disorder (ADHD). Amphetamine sulfate tablets may help increase attention and decrease impulsiveness and hyperactivity in people with ADHD.
- exogenous obesity. Amphetamine sulfate tablets may be used as part of a short-term (a few weeks) weight reduction program for obesity in people who have not responded to other treatment.

Amphetamine sulfate is not for use in children with ADHD under 3 years of age.
It is not known if amphetamine sulfate is safe and effective in children with exogenous obesity under 12 years of age.
Amphetamine sulfate tablets are a federally controlled substance (CII) because it contains amphetamine that can be a target for people who abuse prescription medicines or street drugs. Keep amphetamine sulfate tablets in a safe place to protect it from theft. Never give your amphetamine sulfate tablets to anyone else, because it may cause death or harm them. Selling or giving away amphetamine sulfate tablets may harm others and is against the law.

Do not take amphetamine sulfate tablets if you or your child:

- are allergic to amphetamine products or any of the ingredients in amphetamine sulfate tablets. See the end of this Medication Guide for a complete list of ingredients in amphetamine sulfate tablets.
- are taking or have taken within the past 14 days a medicine used to treat depression called a monoamine oxidase inhibitor (MAOI)

Before taking amphetamine sulfate, tell your healthcare provider about all your or your child's medical conditions, including if you or your child:

- have heart problems, heart disease, heart defects, or high blood pressure
- have mental problems including psychosis, mania, bipolar illness, or depression, or have a family history of suicide, bipolar illness, or depression
- have circulation problems in fingers and toes
- have or have had seizures
- have or had repeated movements or sounds (tics) or Tourette's syndrome, or have a family history of tics or Tourette's syndrome
- are pregnant or plan to become pregnant. It is not known if amphetamine sulfate will harm the unborn baby. Tell your healthcare provider if you or your child become pregnant during treatment with amphetamine sulfate.
- are breastfeeding or plan to breastfeed. Amphetamine sulfate passes into breast milk. You or your child should not breastfeed during treatment with amphetamine sulfate. Talk to your healthcare provider about the best way to feed the baby during treatment with amphetamine sulfate.

Tell your healthcare provider about all of the medicines that you or your child takes, including prescription and over-the-counter medicines, vitamins, and herbal supplements.
Amphetamine sulfate and some medicines may interact with each other and cause serious side effects. Sometimes the doses of other medicines will need to be adjusted during treatment with amphetamine sulfate.
Your healthcare provider will decide if amphetamine sulfate can be taken with other medicines.
Especially tell your healthcare provider if you or your child takes:

- selective serotonin reuptake inhibitors (SSRIs)

- serotonin norepinephrine reuptake inhibitors (SNRIs)

- medicines used to treat migraine headaches called triptans

- tricyclic antidepressants

- lithium

- fentanyl

- tramadol

- tryptophan

- buspirone

- St. John's Wort

Know the medicines that you or your child takes.
Keep a list of your or your child's medicines with you to show your healthcare provider and pharmacist when you or your child get a new medicine.
Do not start any new medicine during treatment with amphetamine sulfate without talking to your doctor first.

How should amphetamine sulfate tablets be taken?

- Take amphetamine sulfate tablets exactly as prescribed by your or your child's healthcare provider.
- Your healthcare provider may change the dose if needed.
- The first dose of the day is usually taken when you first wake up.
- Amphetamine sulfate tablets may cause problems sleeping if taken late in the evening.
- Amphetamine sulfate tablets should be taken 30 to 60 minutes before meals if it is being used to treat exogenous obesity.

If you or your child take too much amphetamine sulfate tablets, call your healthcare provider or Poison Help line at 1-800- 222-1222 or go to the nearest hospital emergency room right away.

What should I avoid while taking amphetamine sulfate tablets?
Do not drive, operate machinery, or do other dangerous activities until you know how amphetamine sulfate affects you.
What are the possible side effects of amphetamine sulfate?

- Amphetamine sulfate may cause serious side effects, including:
- See "What is the most important information I should know about amphetamine sulfate?"
- Slowing of growth (height and weight) in children. Children should have their height and weight checked often during treatment with amphetamine sulfate. Your healthcare provider may stop your child's amphetamine sulfate treatment if they are not growing or gaining weight as expected.
- Seizures. Your healthcare provider may stop treatment with amphetamine sulfate if you or your child have a seizure.
- Circulation problems in fingers and toes (peripheral vasculopathy, including Raynaud's phenomenon). Signs and symptoms may include:
  - fingers or toes may feel numb, cool, painful
  - fingers or toes may change color from pale, to blue, to red

Tell your healthcare provider if you or your child have numbness, pain, skin color change, or sensitivity to temperature in the fingers or toes.
Call your healthcare provider right away if you or your child have any signs of unexplained wounds appearing on fingers or toes during treatment with amphetamine sulfate.

- Serotonin syndrome. This problem may happen when amphetamine sulfate is taken with certain other medicines and may be life-threatening. Call your healthcare provider or go to the nearest hospital emergency room right away if you or your child develop any of the following signs and symptoms of serotonin syndrome:

○ agitation, hallucinations, coma

○ confusion

○ fast heartbeat

○ dizziness

○ flushing

○ muscle stiffness or tightness

○ seizures

○ changes in blood pressure

○ sweating or fever

○ high body temperature (hypothermia)

○ loss of coordination

○ nausea, vomiting, diarrhea

New or worsening tics or worsening Tourette's syndrome. Tell your healthcare provider if you or your child get any new or worsening tics or worsening Tourette's syndrome during treatment with amphetamine sulfate.
The most common side effects of amphetamine sulfate include:

○ headache

○ nervousness

○ itching

○ stomachache

○ dizziness

○ diarrhea or constipation

○ trouble sleeping

○ sexual problems (impotence in males)

○ dry mouth

○ decreased appetite

○ vomiting

○ weight loss

○ unpleasant taste

○ mood swing

These are not all the possible side effects of amphetamine sulfate. Call your doctor for medical advice about side effects. You may report side effects to Lannett Company, Inc. at 1-844-834-0530 or FDA at 1-800-FDA-1088.

How should I store amphetamine sulfate?

- Store amphetamine tablets at room temperature between 68˚F to 77˚F (20˚C to 25˚C).
- Store amphetamine sulfate tablets in a safe place, like a locked cabinet.
- Dispose of remaining, unused, or expired amphetamine sulfate tablets by a medicine take-back program at a U.S. Drug Enforcement Administration (DEA) authorized collection site. If no take-back program or DEA authorized collector is available, mix amphetamine sulfate tablets with an undesirable, nontoxic substance such as dirt, cat litter, or used coffee grounds to make it less appealing to children and pets. Place the mixture in a container such as a sealed plastic bag and throw away amphetamine sulfate tablets in the household trash. Visit www.fda.gov/drugdisposal for additional information on disposal of unused medicines.

Keep amphetamine sulfate tablets and all medicines out of the reach of children.

General information about the safe and effective use of amphetamine sulfate tablets.
Medicines are sometimes prescribed for purposes other than those listed in a Medication Guide. Do not use amphetamine sulfate tablets for a condition for which it was not prescribed. Do not give amphetamine sulfate tablets to other people, even if they have the same symptoms that you or your child have. It may harm them and it is against the law. You can ask your healthcare or pharmacist provider for information about amphetamine sulfate tablets that is written for health professionals.

What are the ingredients in amphetamine sulfate tablets?
Active Ingredient: amphetamine sulfate
Inactive Ingredients: silicified microcrystalline cellulose, crospovidone and stearic acid. The 10 mg tablets also contain FD&C Blue #1 alum lake.
Manufactured by:
Aavis Pharmaceuticals
Hoschton, GA 30548
Distributed by:
Lannett Company, Inc.
Philadelphia, PA 19136
LCI: L7072C
AAV: L7029/03
Rev. 01/2024
For more information about amphetamine sulfate tablets, please contact Lannett Company, Inc. at 1-844-834-0530.

This Medication Guide has been approved by the U.S. Food and Drug Administration.

PACKAGE LABEL

Amphetamine Sulfate 10mg Tablets (CII)